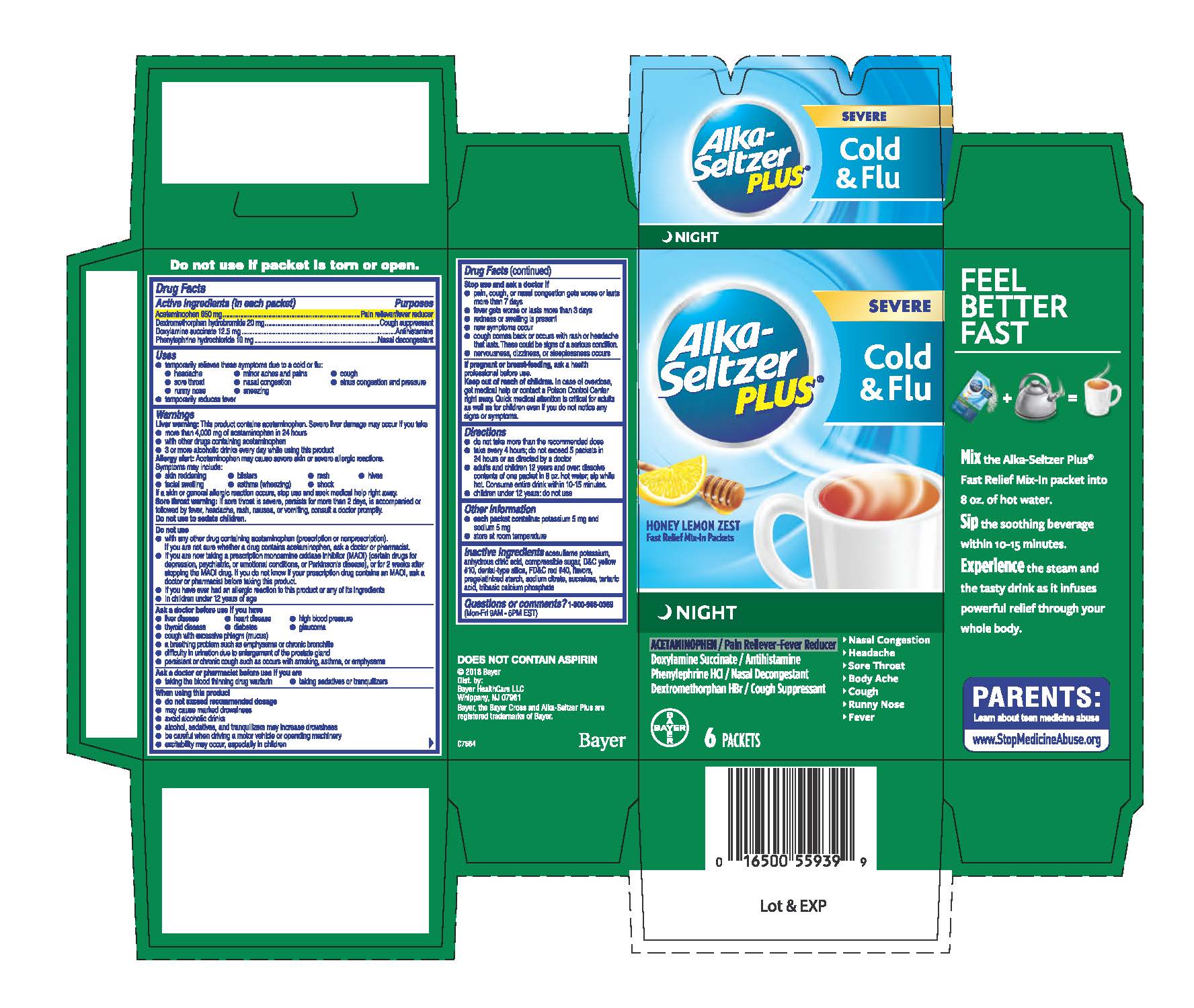 DRUG LABEL: Alka-Seltzer Plus Night Severe Cold and Flu
NDC: 0280-0922 | Form: POWDER, FOR SOLUTION
Manufacturer: Bayer HealthCare LLC.
Category: otc | Type: HUMAN OTC DRUG LABEL
Date: 20260108

ACTIVE INGREDIENTS: ACETAMINOPHEN 650 mg/1 1; DEXTROMETHORPHAN HYDROBROMIDE 20 mg/1 1; DOXYLAMINE SUCCINATE 12.5 mg/1 1; PHENYLEPHRINE HYDROCHLORIDE 10 mg/1 1
INACTIVE INGREDIENTS: ACESULFAME POTASSIUM; ANHYDROUS CITRIC ACID; D&C YELLOW NO. 10; FD&C RED NO. 40; TRISODIUM CITRATE DIHYDRATE; SUCRALOSE; TARTARIC ACID; TRIBASIC CALCIUM PHOSPHATE; STARCH, CORN; SUCROSE; MENTHOL; LEMON; HONEY; SILICON DIOXIDE

Alka-Seltzer Plus® Night Severe Cold + Flu

Drug Facts

ACTIVE INGREDIENT

PURPOSE

Active ingredients (in each packet) | Purposes
Acetaminophen 650 mg | Pain reliever/fever reducer
Dextromethorphan hydrobromide 20 mg | Cough suppressant
Doxylamine succinate 12.5 mg | Antihistamine
Phenylephrine hydrochloride 10 mg | Nasal decongestant

Uses

- temporarily relieves these symptoms due to a cold or flu:
  - headache
  - minor aches and pains
  - cough
  - sore throat
  - nasal congestion
  - sinus congestion and pressure
  - runny nose
  - sneezing
- temporarily reduces fever

Warnings

Liver warning

This product contains acetaminophen. Severe liver damage may occur if you take

- more than 5 packets in 24 hours, which is the maximum daily amount for this product
- with other drugs containing acetaminophen
- 3 or more alcoholic drinks every day while using this product

Sore throat warning

If sore throat is severe, persists for more than 2 days, is accompanied or followed by fever, headache, rash, nausea, or vomiting, consult a doctor promptly.

Do not use to sedate children.

Do not use

- with any other drug containing acetaminophen (prescription or nonprescription). If you are not sure whether a drug contains acetaminophen, ask a doctor or pharmacist.
- if you are now taking a prescription monoamine oxidase inhibitor (MAOI) (certain drugs for depression, psychiatric, or emotional conditions, or Parkinson's disease), or for 2 weeks after stopping the MAOI drug. If you do not know if your prescription drug contains an MAOI, ask a doctor or pharmacist before taking this product.
- if you have ever had an allergic reaction to this product or any of its ingredients
- in children under 12 years of age

Ask a doctor before use if you have

- liver disease
- heart disease
- high blood pressure
- thyroid disease
- diabetes
- glaucoma
- cough with excessive phlegm (mucus)
- a breathing problem such as emphysema or chronic bronchitis
- difficulty in urination due to enlargement of the prostate gland
- persistent or chronic cough such as occurs with smoking, asthma, or emphysema

Ask a doctor or pharmacist before use if you are

- taking the blood thinning drug warfarin
- taking sedatives or tranquilizers

When using this product

- do not exceed recommended dosage
- may cause marked drowsiness
- avoid alcoholic drinks
- alcohol, sedatives, and tranquilizers may increase drowsiness
- be careful when driving a motor vehicle or operating machinery
- excitability may occur, especially in children

Stop use and ask a doctor if

- pain, cough, or nasal congestion gets worse or lasts more than 7 days
- fever gets worse or lasts more than 3 days
- redness or swelling is present
- new symptoms occur
- cough comes back or occurs with rash or headache that lasts. These could be signs of a serious condition.
- nervousness, dizziness, or sleeplessness occurs

PREGNANCY OR BREAST FEEDING

If pregnant or breast-feeding, ask a health professional before use.

Keep out of reach of children. In case of overdose, get medical help or contact a Poison Control Center right away. Quick medical attention is critical for adults as well as for children even if you do not notice any signs or symptoms.

Directions

- do not take more than the recommended dose
- take every 4 hours; do not exceed 5 packets in 24 hours or as directed by a doctor
- adults and children 12 years and over: dissolve contents of one packet in 8 oz. hot water; sip while hot. Consume entire drink within 10-15 minutes.
- children under 12 years: do not use

Other information

- each packet contains: potassium 5 mg and sodium 5 mg
- store at room temperature

Inactive ingredients

acesulfame potassium, anhydrous citric acid, compressible sugar, D&C yellow #10, dental-type silica, FD&C red #40, flavors, pregelatinized starch, sodium citrate, sucralose, tartaric acid, tribasic calcium phosphate

Questions or comments?

1-800-986-0369
(Mon-Fri 9AM - 5PM EST)

Dist. by: Bayer HealthCare LLC
Whippany, NJ 07981

PRINCIPAL DISPLAY PANEL - 6 Packet Carton

Alka-Seltzer PLUS ®

Severe

Cold & Flu

Honey Lemon Zest

Fast Relief Mix-In Packets

Night

Acetaminophen / Pain reliever-fever reducer
Doxylamine succinate / Antihistamine
Phenylephrine HCl / Nasal decongestant
Dextromethorphan HBr / Cough suppressant

• Nasal Congestion

• Headache

• Sore Throat

• Body Ache
• Cough

• Runny Nose

• Fever

6 PACKETS